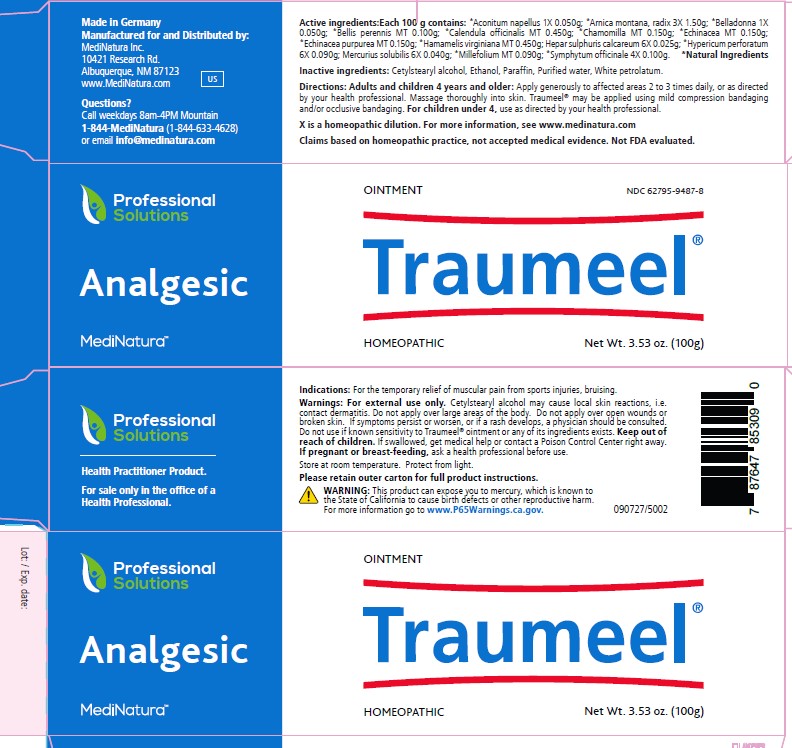 DRUG LABEL: Traumeel
NDC: 62795-9487 | Form: OINTMENT
Manufacturer: MediNatura Inc
Category: homeopathic | Type: HUMAN OTC DRUG LABEL
Date: 20230926

ACTIVE INGREDIENTS: ACONITUM NAPELLUS 1 [hp_X]/1 g; ARNICA MONTANA ROOT 3 [hp_X]/1 g; ATROPA BELLADONNA 1 [hp_X]/1 g; BELLIS PERENNIS 1 [hp_X]/1 g; CALENDULA OFFICINALIS FLOWERING TOP 1 [hp_X]/1 g; MATRICARIA RECUTITA 1 [hp_X]/1 g; ECHINACEA, UNSPECIFIED 1 [hp_X]/1 g; ECHINACEA PURPUREA 1 [hp_X]/1 g; HAMAMELIS VIRGINIANA ROOT BARK/STEM BARK 1 [hp_X]/1 g; CALCIUM SULFIDE 6 [hp_X]/1 g; HYPERICUM PERFORATUM 6 [hp_X]/1 g; MERCURIUS SOLUBILIS 6 [hp_X]/1 g; ACHILLEA MILLEFOLIUM 1 [hp_X]/1 g; COMFREY ROOT 4 [hp_X]/1 g
INACTIVE INGREDIENTS: CETOSTEARYL ALCOHOL; ALCOHOL; WATER; PARAFFIN; MINERAL OIL

Traumeel Ointment

ACTIVE INGREDIENTS

Active ingredients: Each 100 g contains:

*Aconitum napellus 1X 0.050g; *Arnica montana, radix 3X 1.50g; *Belladonna 1X 0.050g; *Bellis perennis MT 0.100g; *Calendula officinalis MT 0.450g; *Chamomilla MT 0.150g; *Echinacea MT 0.150g; *Echinacea purpurea MT 0.150g; *Hamamelis virginiana MT 0.450g; Hepar sulphuris calcareum 6X 0.025g; *Hypericum perforatum 6X 0.090g; Mercurius solubilis 6X 0.040g; *Millefolium MT 0.090g; *Symphytum officinale 4X 0.100g.

*Natural Ingredients

PURPOSE

Analgesic

Warning

Warnings: For external use only. Cetylstearyl alcohol may cause local skin reactions, i.e.
contact dermatitis. Do not apply over large areas of the body. Do not apply over open wounds or
broken skin. If symptoms persist or worsen, or if a rash develops, a physician should be consulted.
Do not use if known sensitivity to Traumeel® ointment or any of its ingredients exists. Keep out of
reach of children. If swallowed, get medical help or contact a Poison Control Center right away.
If pregnant or breast-feeding, ask a health professional before use.
Store at room temperature. Protect from light.
Please retain outer carton for full product instructions.
WARNING: This product can expose you to mercury, which is known to
the State of California to cause birth defects or other reproductive harm.
For more information go to www.P65Warnings.ca.gov.

Directions

Directions: Adults and children 4 years and older: Apply generously to affected areas 2 to 3 times daily, or as directed
by your health professional. Massage thoroughly into skin. Traumeel® may be applied using mild compression bandaging
and/or occlusive bandaging. For children under 4, use as directed by your health professional.

INACTIVE INGREDIENTS

Paraffin, liquid, Cetostearyl alcohol (type A), emulsifying, Paraffin, white soft, Ethanol (96 per cent)

KEEP OUT OF REACH OF CHILDREN

Indications

For the temporary relief of muscular pain from sports injuries, bruising.

PACKAGE LABEL

Add image transcription here...